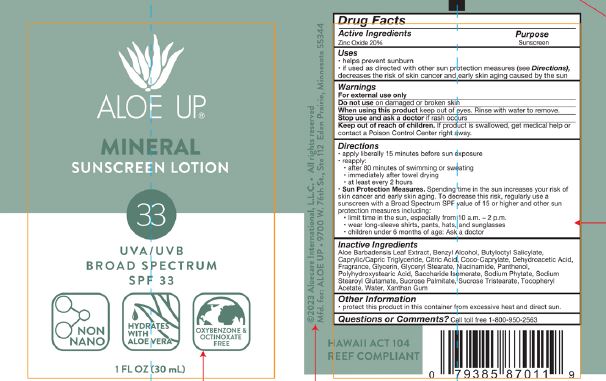 DRUG LABEL: Aloe UP SPF 33 Mineral
NDC: 61477-231 | Form: LOTION
Manufacturer: Aloe Care International, LLC
Category: otc | Type: HUMAN OTC DRUG LABEL
Date: 20251224

ACTIVE INGREDIENTS: ZINC OXIDE 20 g/100 g
INACTIVE INGREDIENTS: COCO-CAPRYLATE; DEHYDROACETIC ACID; FRAGRANCE 13576; GLYCERIN; GLYCERYL STEARATE; NIACINAMIDE; POLYHYDROXYSTEARIC ACID (2300 MW); SACCHARIDE ISOMERATE; SUCROSE PALMITATE; WATER; BENZYL ALCOHOL; ALOE BARBADENSIS LEAF JUICE; CITRIC ACID; SUCROSE TRISTEARATE; XANTHAN GUM; SODIUM PHYTATE; SODIUM STEAROYL GLUTAMATE; PANTHENOL; .ALPHA.-TOCOPHEROL ACETATE; BUTYLOCTYL SALICYLATE; CAPRYLIC/CAPRIC TRIGLYCERIDE

Aloe UP SPF 33 Mineral Sunscreen Lotion 1 oz & 3 oz & 1 gal

ACTIVE INGREDIENT

Zinc Oxide 20%

PURPOSE

Sunscreen

INDICATIONS AND USAGE

- helps prevent sunburn
- if used as directed with other sun protection measures (see Directions), decreases the risk of skin cancer and arly skin aging caused by the sun.

WARNINGS

For external use only

Do not use on damaged or broken skin

When using this product keep out of eyes. Rinse with water to remove.

Stop use and ask a doctor if rash occurs.

Keep out of reach of children. If product is swallowed, get medical help or contact a Poison Control Center right away.

DOSAGE AND ADMINISTRATION

- apply liberally 15 minutes before sun exposure
- reapply:
- after 80 minutes of swimming or sweating
- immediately after towel drying
- at least every 2 hours
- Sun Protection Measures.Spending time in the sun increases your risk of skin cancer and early skin aging. To decrease the risk, reguarly use a susncreen with a Broad Spectrum SPF value of 15 or higher and other sun protection measures including:
- limit time in the sun, especially from 10am - 2pm.
- wear long-sleeve shirts, pants, hats, and sunglasses
- children under 6 months of age: Ask a doctor

OTHER SAFETY INFORMATION

Protect this product in this container from excessive heat and direct sun.

INACTIVE INGREDIENT

Aloe Barbadensis Leaf Juice

Benzyl alcohol

Butyloctyl Salicylate

Caprylic/Capric Triglyceride

Citric Acid

Coco-Caprylate

Coconut Mango Fragrance

Dehydroacetic acid

Glycerin

Glyceryl Stearate

Niacinamide

Panthenol

Polyhydroxystearic Acid

Saccharide Isomerate

Sodium Phytate

Sodium Stearoyl Glutamate

Sucrose Tristearate

Sucrose Palmitate

Tocopheryl acetate

Water

Xanthan gum

Questions or Comments?

Call toll free 1-800-950-2563